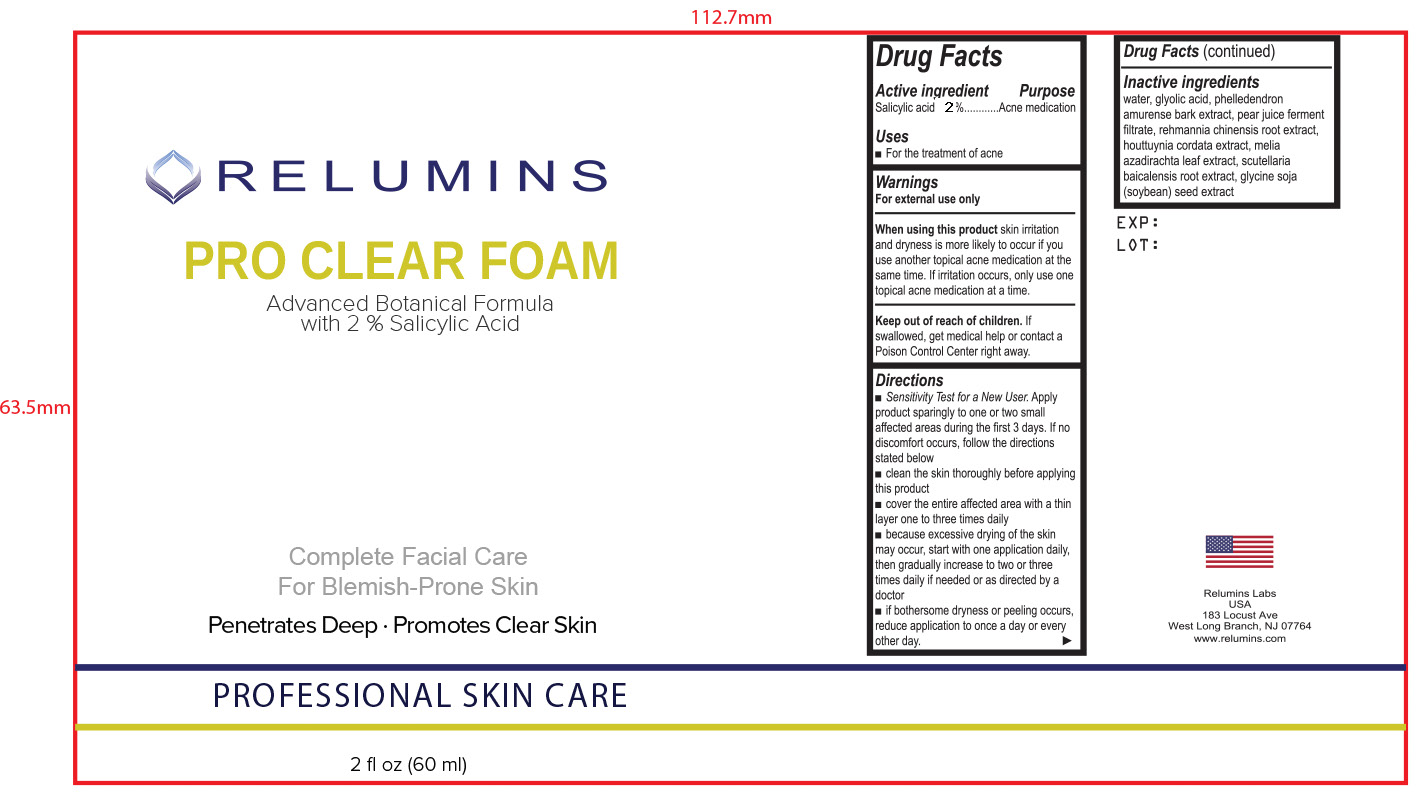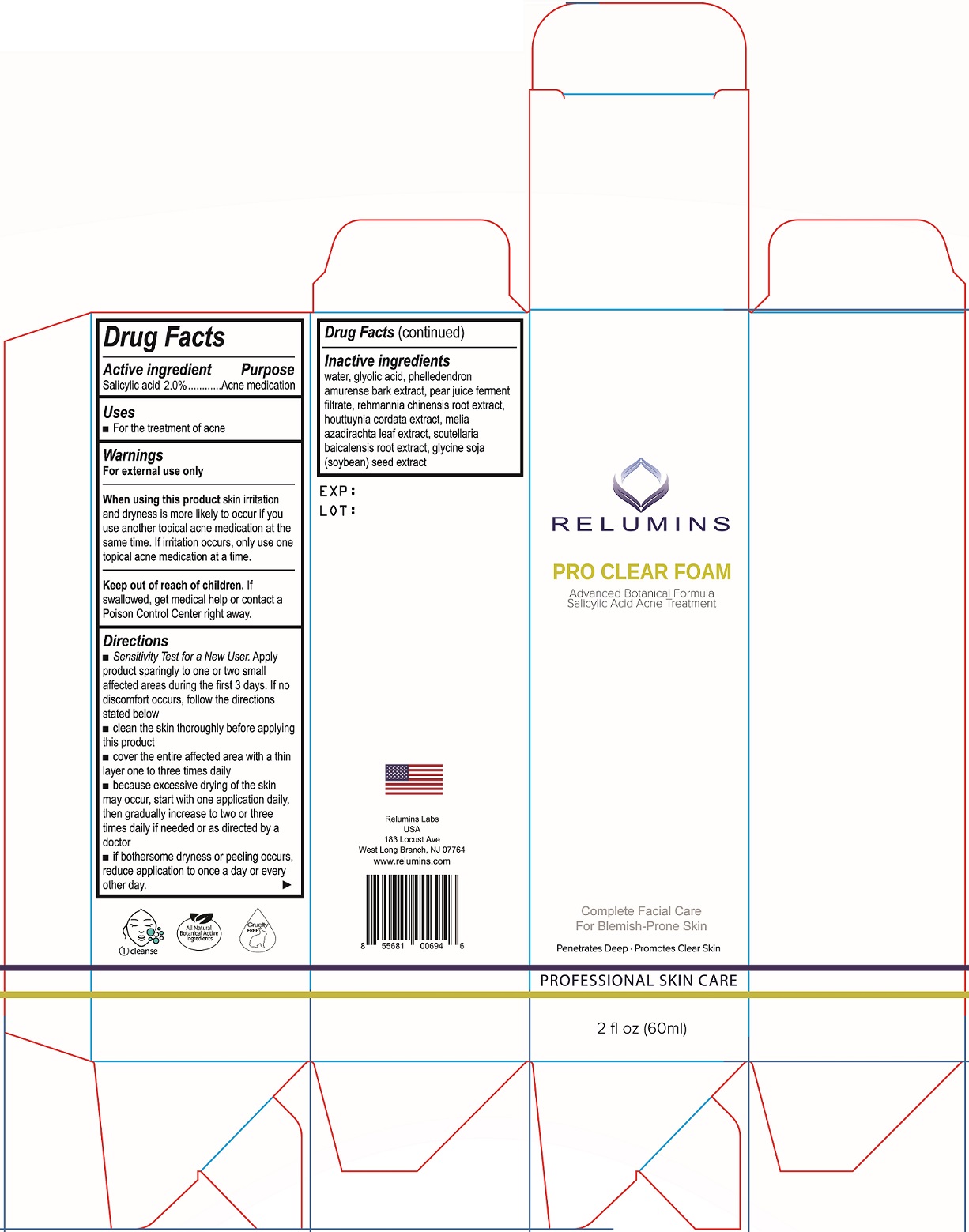 DRUG LABEL: Pro Clear Foam
NDC: 79061-042 | Form: LIQUID
Manufacturer: RELUMINS LABS LLC
Category: otc | Type: HUMAN OTC DRUG LABEL
Date: 20210701

ACTIVE INGREDIENTS: SALICYLIC ACID 2 mg/100 mL
INACTIVE INGREDIENTS: WATER; GLYCOLIC ACID; PHELLODENDRON AMURENSE BARK; PEAR JUICE; REHMANNIA GLUTINOSA ROOT; HOUTTUYNIA CORDATA FLOWERING TOP; AZADIRACHTA INDICA LEAF; SCUTELLARIA BAICALENSIS ROOT; SOYBEAN

Active ingredient

Salicylic acid 2.0%

Purpose

Acne medication

Uses

- For the treatment of acne

Warnings

For external use only

When using this product skin irritation and dryness is more likely to occur if you use another topical acne medication at the same time. If irritation occurs, only use one topical acne medication at a time.

Keep out of reach of children. If swallowed, get medical help or contact a Poison Control Center right away.

Directions

- Sensitivity Test for a New User. Apply product sparingly to one or two small affected areas during the first 3 days. If no discomfort occurs, follow the directions stated below
- clean the skin thoroughly before applying this product
- cover the entire affected area with a thin layer one to three times daily
- because excessive drying of the skin may occur, start with one application daily, then gradually increase to two or three times daily if needed or as directed by a doctor
- if bothersome dryness or peeling occurs, reduce application to once a day or every other day.

Inactive ingredients

water, glyolic acid, phelledendron amurense bark extract, pear juice ferment filtrate, rehmannia chinensis root extract, houttuynia cordata extract, melia azadirachta leaf extract, scutellaria baicalensis root extract, glycine soja (soybean) seed extract

Package Labels - 2 fl oz (60 mL) - NDC 79061-042-01

Bottle Label

RELUMINS

PRO CLEAR FOAM

Advanced Botanical Formula with 2% Salicylic Acid

Complete Facial Care For Blemish-Prone Skin

Penetrates Deep • Promotes Clear Skin

PROFESSIONAL SKIN CARE

2 fl oz (60 ml)

EXP:

LOT:

Relumins Labs

USA

183 Locust Ave

West Long Branch, NJ 07764

www.relumins.com

Carton Label

RELUMINS

PRO CLEAR FOAM

Advanced Botanical Formula

Salicylic Acid Acne Treatment

Complete Facial Care For Blemish-Prone Skin

Penetrates Deep • Promotes Clear Skin

PROFESSIONAL SKIN CARE

2 fl oz (60 ml)

EXP:

LOT:

Relumins Labs

USA

183 Locust Ave

West Long Branch, NJ 07764

www.relumins.com